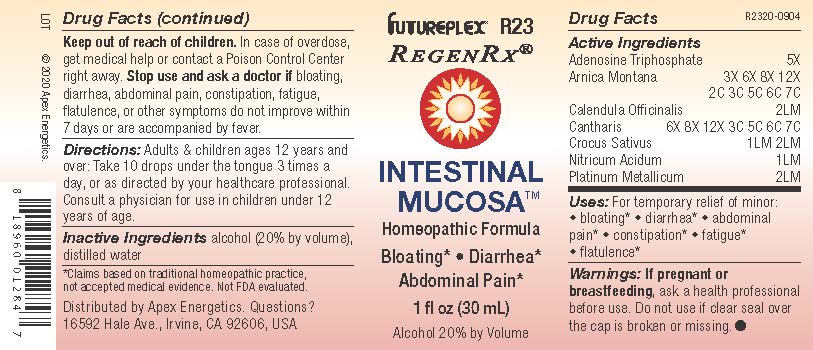 DRUG LABEL: R23
NDC: 63479-1823 | Form: SOLUTION/ DROPS
Manufacturer: Apex Energetics Inc.
Category: homeopathic | Type: HUMAN OTC DRUG LABEL
Date: 20240108

ACTIVE INGREDIENTS: ADENOSINE TRIPHOSPHATE 5 [hp_X]/1 mL; ARNICA MONTANA 7 [hp_C]/1 mL; LYTTA VESICATORIA 7 [hp_C]/1 mL; PLATINUM 2 [hp_Q]/1 mL; CALENDULA OFFICINALIS FLOWERING TOP 2 [hp_Q]/1 mL; SAFFRON 2 [hp_Q]/1 mL; NITRIC ACID 1 [hp_Q]/1 mL
INACTIVE INGREDIENTS: ALCOHOL; WATER

R23

Active Ingredients
Adenosine Triphosphate | 5X
Arnica Montana | 3X 6X 8X 12X 2C 3C 5C 6C 7C
Calendula Officinalis | 2LM
Cantharis | 6X 8X 12X 3C 5C 6C 7C
Crocus Sativus | 1LM 2LM
Nitricum Acidum | 1LM
Platinum Metallicum | 2LM

INDICATIONS AND USAGE

Uses:

For temporary relief of minor:

bloating*

diarrhea*

abdominal pain*

constipation*

fatigue*

flatulence*

*Claims based on traditional homeopathic practice, not accepted medical evidence. Not FDA evaluated.

Warnings:

PREGNANCY OR BREAST FEEDING

If pregnant or breastfeeding, ask a health professional before use.

Do not use if clear seal over the cap is broken or missing.

Keep out of reach of children. In case of overdose, get medical help or contact a Poison Control Center right away.

Stop use and ask a doctor if bloating, diarrhea, abdominal pain, constipation, fatigue, flatulence, or other symptoms do not improve within 7 days or are accompanied by fever.

Directions:

Adults & children ages 12 years and over: Take 10 drops under the tongue 3 times a day, or as directed by your healthcare professional. Consult a physician for use in children under 12 years of age.

Inactive Ingredients

alcohol (20% by volume), distilled water

Distributed by Apex Energetics. Questions?

16592 Hale Ave., Irvine, CA 92606, USA

PACKAGE LABEL

FUTUREPLEX® R23

REGENRX®

INTESTINAL MUCOSA™

Homeopathic Formula

Bloating* Diarrhea*

Abdominal Pain*

1 fl oz (30 mL)

Alcohol 20% by Volume